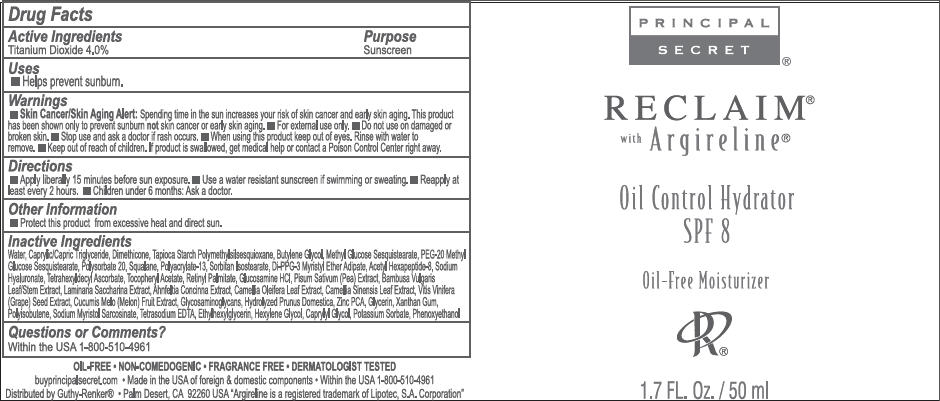 DRUG LABEL: Principal Secret Reclaim Oil Control hydrator SPF-8
NDC: 70605-028 | Form: CREAM
Manufacturer: Guthy-Renker LLC
Category: otc | Type: HUMAN OTC DRUG LABEL
Date: 20240108

ACTIVE INGREDIENTS: Titanium Dioxide 4 mg/100 mL
INACTIVE INGREDIENTS: Water; MEDIUM-CHAIN TRIGLYCERIDES; Dimethicone; Butylene Glycol; Methyl Glucose Sesquistearate; PEG-20 METHYL GLUCOSE SESQUISTEARATE; Polysorbate 20; Squalane; POLYACRYLAMIDE (1500 MW); Sorbitan Isostearate; Di-PPG-3 Myristyl Ether Adipate; Acetyl Hexapeptide-8; HYALURONATE SODIUM; Tetrahexyldecyl Ascorbate; .ALPHA.-TOCOPHEROL ACETATE; VITAMIN A PALMITATE; GLUCOSAMINE HYDROCHLORIDE; PEA; BAMBUSA VULGARIS TOP; SACCHARINA LATISSIMA; AHNFELTIOPSIS CONCINNA; CAMELLIA OLEIFERA LEAF; GREEN TEA LEAF; VITIS VINIFERA SEED; MUSKMELON; ZINC PIDOLATE; Glycerin; Xanthan Gum; POLYISOBUTYLENE (1000 MW); SODIUM MYRISTOYL SARCOSINATE; EDETATE SODIUM; Ethylhexylglycerin; Hexylene Glycol; Caprylyl Glycol; Potassium Sorbate; Phenoxyethanol

Principal Secret® Reclaim® Oil Control hydrator SPF-8

Drug Fact Label

Active ingredient

Titanium Dioxide 4.0%

Purpose

Sunscreen

Uses

- Helps prevent sunburn

Warnings

- Skin Cancer/Skin Aging Alert: Spending time in the sun increases your risk of skin cancer and early skin aging. This product has been shown only to prevent sunburn not skin cancer or early skin aging.
- For external use only.

- Do not use on damaged or broken skin.

- Stop use and ask a doctor if rash occurs.

- When using this product keep out of eyes.
- Rinse with water to remove.

- Keep out of reach of children. If product is swallowed, get medical help or contact a Poison Control Center right away.

Directions

- Apply liberally 15 minutes before sun exposure.
- Use a water-resistant sunscreen if swimming or sweating.
- Reapply at least every 2 hours.
- Children under 6 months: Ask a doctor.

Other Information

- Protect this product from excessive heat and direct sun.

Inactive ingredients

Water, Caprylic/Capric Triglyceride, Dimethicone, Tapioca Starch Polymethylsilsesquioxane, Butylene Glycol, Methyl Glucose Sesquistearate, PEG-20 Methyl Glucose Sesquistearate, Polysorbate 20, Squalane, Polyacrylate-13, Sorbitan Isostearate, Di-PPG-3 Myristyl Ether Adipate, Acetyl Hexapeptide-8, Sodium Hyaluronate, Tetrahexyldecyl Ascorbate, Tocopheryl Acetate, Retinyl Palmitate, Glucosamine HCl, Pisum Sativum (Pea) Extract, Bambusa Vulgaris Leaf/Stem Extract, Laminaria Saccharina Extract, Ahnfeltia Concinna Extract, Camellia Oleifera Leaf Extract, Camellia Sinensis Leaf Extract, Vitis Vinifera (Grape) Seed Extract, Cucumis Melo (Melon) Fruit Extract, Glycosaminoglycans, Hydrolyzed Prunus Domestica, Zinc PCA, Glycerin, Xanthan Gum, Polyisobutene, Sodium Myristol Sarcosinate, Tetrasodium EDTA, Ethylhexylglycerin, Hexylene Glycol, Caprylyl Glycol, Potassium Sorbate, Phenoxyethanol

Questions or comments?

Within US 1-800-510-4961

Distributed by Guthy-Renker® • Palm Desert, CA 92260 USA

PRINCIPAL DISPLAY PANEL - 50 mL Bottle Label

PRINCIPAL
SECRET®

RECLAIM®
with Argireline®

Oil Control Hydrator
SPF 8

Oil-Free Moisturizer

1.7 FL. Oz. / 50 ml